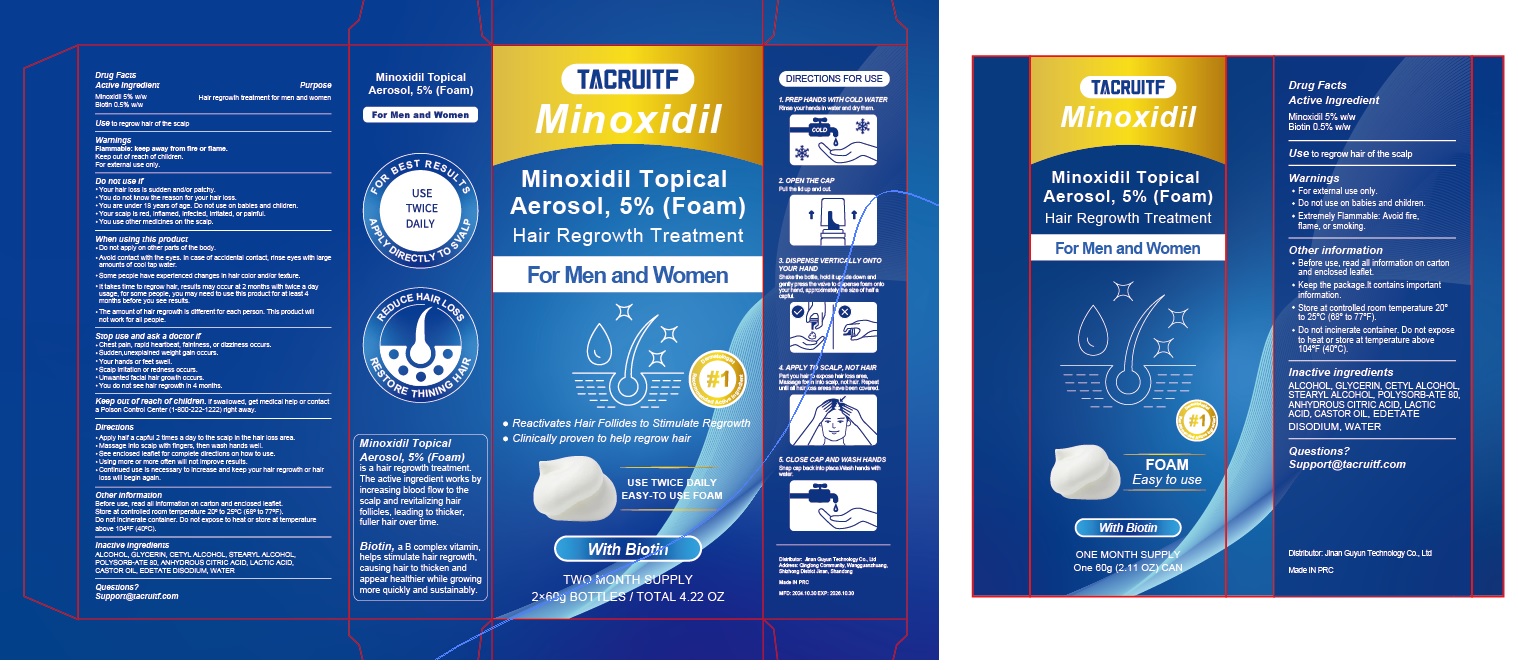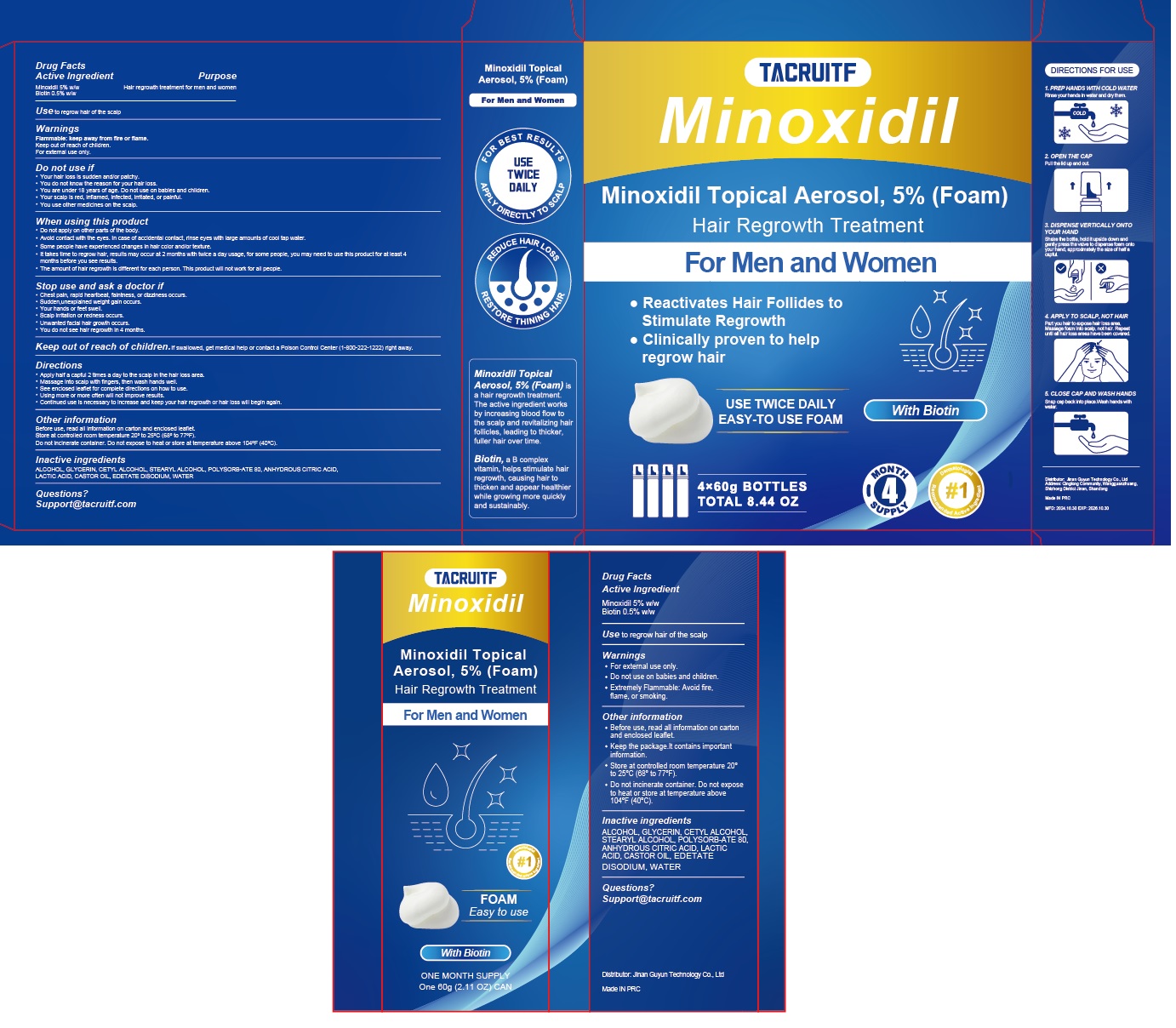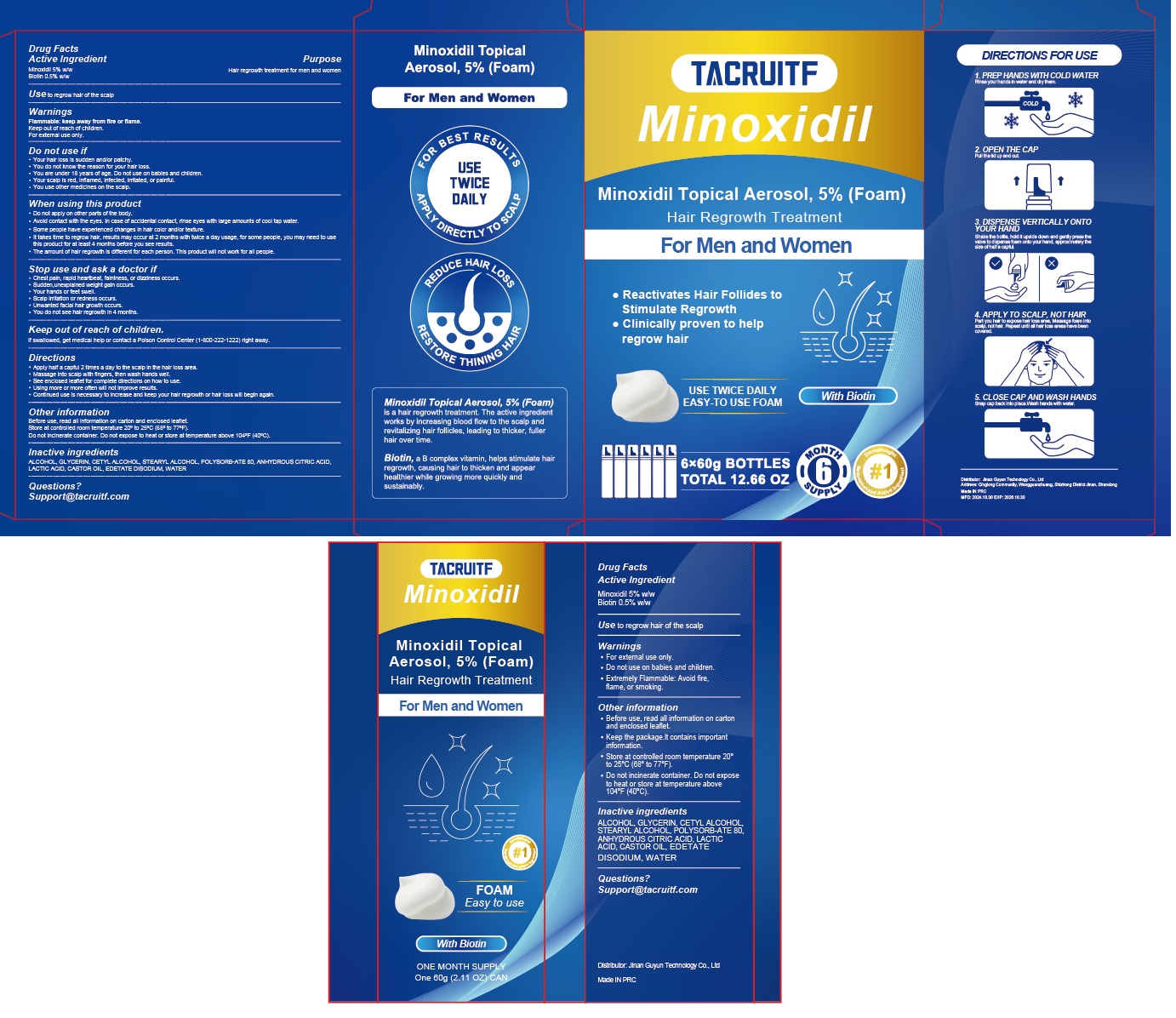 DRUG LABEL: 5% Minoxidil Hair Growth Foam with Biotin
NDC: 83988-002 | Form: AEROSOL, FOAM
Manufacturer: Jinan Guyun Technology Co., Ltd
Category: otc | Type: HUMAN OTC DRUG LABEL
Date: 20241030

ACTIVE INGREDIENTS: MINOXIDIL 5 g/100 g; BIOTIN 0.5 g/100 g
INACTIVE INGREDIENTS: POLYSORBATE 80; BUTANE; WATER; CETYL ALCOHOL; EDETATE DISODIUM; CASTOR OIL; ALCOHOL; LACTIC ACID; STEARYL ALCOHOL; ISOBUTANE; GLYCERIN; ANHYDROUS CITRIC ACID

5% Minoxidil Hair Growth Foam with Biotin

5% Minoxidil Hair Growth Foam with Biotin

ACTIVE INGREDIENT

Minoxidil 5%
Biotin 0.5%

PURPOSE

Hair regrowth treatment for men and women

INDICATIONS AND USAGE

Use to regrow hair of the scalp

WARNINGS

Flammable: keep away from fire or flame.

Keep out of reach of children.

For external use only

DO NOT USE

Your hair loss is sudden and/or patchy.
You do not know the reason for your hair loss.
You are under 18 years of age. Do not use on babies and children.
Your scalp is red, inflamed, infected, irritated, or painful.
You use other medicines on the scalp.

WHEN USING

Do not apply on other parts of the body.

Avoid contact with the eyes. In case of accidental contact, rinse eyes with largeamounts of cool tap water.
Some people have experienced changes in hair color and/or texture
It takes time to regrow hair, results may occur at 2 months with twice a davusage, for some people, you may need to use this product for at least 4months before you see results.
The amount of hair regrowth is different for each person. This product willnot work for all people.

STOP USE

Chest pain, rapid heartbeat, faintness, or dizziness occurs.
Sudden,unexplained weight gain occurs.
Your hands or feet swell.
Scalp irritation or redness occurs.
Unwanted facial hair growth occurs,
You do not see hair regrowth in 4 months,

Keep out of reach of children. lf swallowed, get medical help or contact
a Poison Control Center(1-800-222-1222)right away.

DOSAGE AND ADMINISTRATION

Apply half a capful 2 times a day to the scalp in the hair loss area.

Massage into scalp with fingers, then wash hands well.

See enclosed leaflet for complete directions on how to use.

Using more or more often will not improve results.

Continued use is necessary to increase and keep your hair regrowth or hairloss will begin again.

STORAGE AND HANDLING

Before use, read all information on carton and enclosed leaflet.Store at controlled room temperature 20° to 25°℃ (68° to 77°F)Do not incinerate container. Do not expose to heat or store at temperatureabove 104°F(40°C)

INACTIVE INGREDIENT

ALCOHOL
GLYCERIN
CETYL ALCOHOL
STEARYL ALCOHOL
POLYSORBATE 80
ANHYDROUS CITRIC ACID
LACTIC ACID
CASTOR OIL
EDETATE DISODIUM
ISOBUTANE
BUTANE
WATER